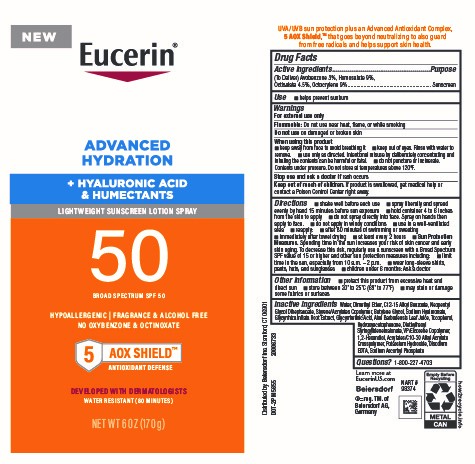 DRUG LABEL: Eucerin Advanced Hydration Sunscreen SPF 50
NDC: 66800-0000 | Form: AEROSOL, SPRAY
Manufacturer: Beiersdorf Inc
Category: otc | Type: HUMAN OTC DRUG LABEL
Date: 20251231

ACTIVE INGREDIENTS: HOMOSALATE 9 g/100 g; OCTOCRYLENE 9 g/100 g; AVOBENZONE 3 g/100 g; OCTISALATE 4.5 g/100 g
INACTIVE INGREDIENTS: DIMETHYL ETHER; ALKYL (C12-15) BENZOATE; WATER; NEOPENTYL GLYCOL DIHEPTANOATE; BUTYLENE GLYCOL; HYALURONATE SODIUM; GLYCYRRHIZA INFLATA ROOT; ALOE VERA LEAF; STYRENE/ACRYLAMIDE COPOLYMER (MW 500000); TOCOPHEROL; VINYLPYRROLIDONE/EICOSENE COPOLYMER; CARBOMER INTERPOLYMER TYPE A (ALLYL SUCROSE CROSSLINKED); EDETATE DISODIUM; ENOXOLONE; HYDROXYACETOPHENONE; DIETHYLHEXYL SYRINGYLIDENEMALONATE; 1,2-HEXANEDIOL; SODIUM ASCORBYL PHOSPHATE; POTASSIUM HYDROXIDE

Eucerin Advanced Hydration Spray Lotion Sunscreen SPF 50

Active ingredients

(To Deliver) Avobenzone 3%, Homosalate 9%, Octisalate 4.5%, Octocrylene 9%

Purpose

Sunscreen

Uses

■ helps prevent sunburn

■ if used as directed with other sun protection measures (see Directions), decreases the risk of skin cancer and early skin aging caused by the sun

Warnings

For external use only

Flammable:Do not use near heat, flame, or while smoking

Do not useon damaged or broken skin

When using this product
■ keep away from face to avoid breathing it

■ keep out of eyes. Rinse with water to remove.

■ use only as directed. Intentional misuse by deliberately concentrating and inhaling
the contents can be harmful or fatal.

■ do not puncture or incinerate. Contents under pressure. Do not store at temperatures above 120°F.

Stop use and ask a doctor ifrash occurs

Keep out of reach of children.If product is swallowed, get medical help or contact a Poison Control Center right away.

Directions

■ shake well before each use

■ spray liberally and spread evenly by hand 15 minutes before sun exposure

■ hold container 4 to 6 inches from the skin to apply

■ do not spray directly into face. Spray on hands then apply to face.

■ do not apply in windy conditions

■ use in a well-ventilated area

■ reapply:

■ after 80 minutes of swimming or sweating

■ immediately after towel drying

■ at least every 2 hours

■ Sun Protection Measures.Spending time in the sun increases your risk of skin cancer and early skin aging. To decrease this risk, regularly use a sunscreen with a Broad Spectrum SPF value of 15 or higher and other sun protection measures including:

■ limit time in the sun, especially from 10 a.m. – 2 p.m.

■ wear long-sleeve shirts, pants, hats, and sunglasses

■ children under 6 months: Ask a doctor

Other information

■ protect this product from excessive heat and direct sun

■ store between 20° to 25°C (68° to 77°F)

■ may stain or damage some fabrics or surfaces

Inactive ingredients

Water, Dimethyl Ether, C12-15 Alkyl Benzoate, Neopentyl Glycol Diheptanoate, Styrene/Acrylates Copolymer, Butylene Glycol, Sodium Hyaluronate, Glycyrrhiza Inflata Root Extract, Glycyrrhetinic Acid, Aloe Barbadensis Leaf Juice, Tocopherol, Hydroxyacetophenone, Diethylhexyl Syringylidenemalonate, VP/Eicosene Copolymer, 1,2-Hexandiol, Acrylates/C10-30 Alkyl Acrylate Crosspolymer, Potassium Hydroxide, Disodium EDTA, Sodium Ascorbyl Phosphate

Questions?

1-866-277-4703

PACKAGE LABEL

Eucerin®

Advanced Hydration

+Hyaluronic Acid & Humectants

Lightweight Sunscreen Lotion Spray

50Broad Spectrum SPF 50

Hypoallergenic|Fragrance & Alcohol Free

No Oxybenzone & Octinoxate

5 AOX SHIELD Antioxidant Defense

Developed with Dermatologists

Water Resistant (80 Minutes)

Net Wt 6 oz (170 g)